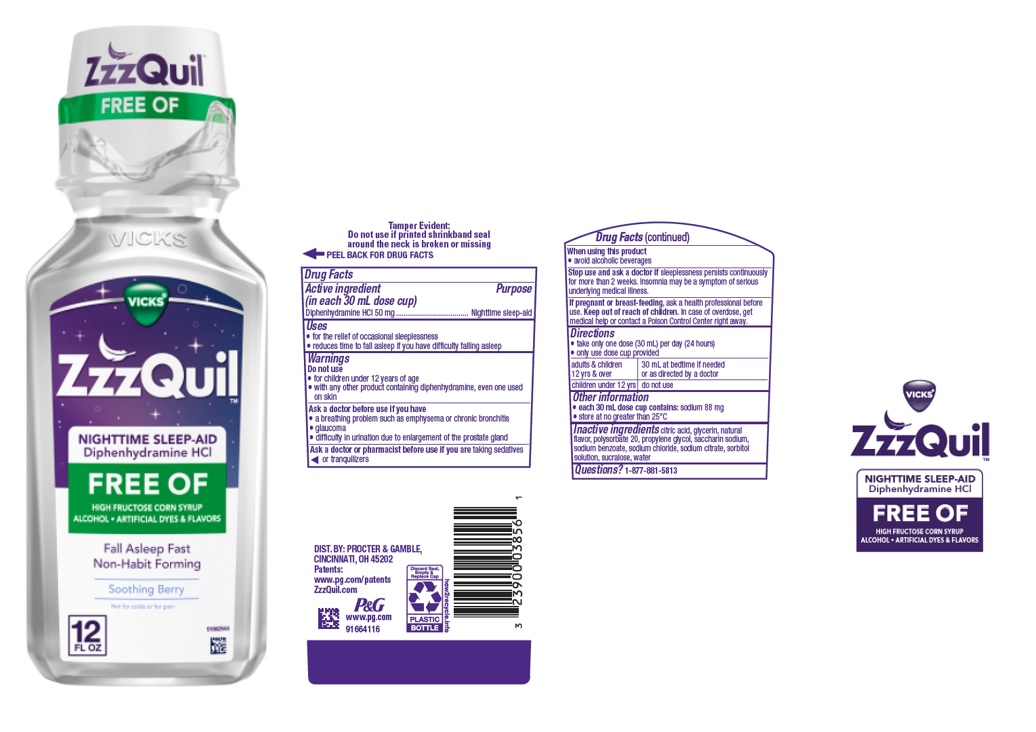 DRUG LABEL: VICKS ZzzQuil
NDC: 69423-795 | Form: LIQUID
Manufacturer: The Procter & Gamble Manufacturing Company
Category: otc | Type: HUMAN OTC DRUG LABEL
Date: 20251003

ACTIVE INGREDIENTS: DIPHENHYDRAMINE HYDROCHLORIDE 50 mg/30 mL
INACTIVE INGREDIENTS: SODIUM BENZOATE; ANHYDROUS CITRIC ACID; WATER; SACCHARIN SODIUM; SODIUM CITRATE; GLYCERIN; SORBITOL; SUCRALOSE; POLYSORBATE 20; PROPYLENE GLYCOL; SODIUM CHLORIDE

Vicks ZzzQuil™
Nighttime Sleep-Aid
Diphenhydramine HCl
FREE OF

Drug Facts

Active ingredient (in each 30 mL dose cup)

Diphenhydramine HCl 50 mg

Purpose

Nighttime sleep-aid

Uses

- for the relief of occasional sleeplessness
- reduces time to fall asleep if you have difficulty falling asleep

Warnings

Do not use

- for children under 12 years of age
- with any other product containing diphenhydramine, even one used on skin

Ask a doctor before use if you have

- a breathing problem such as emphysema or chronic bronchitis
- glaucoma
- difficulty in urination due to enlargement of the prostate gland

Ask a doctor or pharmacist before use if you are

taking sedatives or tranquilizers

When using this product

- avoid alcoholic beverages

Stop use and ask a doctor if

sleeplessness persists continuously for more than 2 weeks. Insomnia may be a symptom of a serious underlying medical illness.

If pregnant or breast-feeding,

ask a health professional before use.

Keep out of reach of children.

OVERDOSAGE

In case of overdose, get medical help or contact a Poison Control Center right away.

Directions

- take only one dose (30 mL) per day (24 hours)
- only use dose cup provided

adults & children 12 yrs & over | 30 mL at bedtime if needed or as directed by a doctor
children under 12 yrs | do not use

Other information

- each 30 mL dose cup contains: sodium 88 mg
- store at no greater than 25°C

Inactive ingredients

citric acid, glycerin, natural flavor, polysorbate 20, propylene glycol, saccharin sodium, sodium benzoate, sodium chloride, sodium citrate, sorbitol solution, sucralose, water

Questions or comments?

1-877-881-5813

Tamper Evident: Do not use if printed shrinkband seal around the neck is broken or missing.

DIST. BY: PROCTER & GAMBLE

CINCINNATI, OH 45202

PRINCIPAL DISPLAY PANEL

Vicks®

ZzzQuil™

Nighttime Sleep-Aid

Diphenhydramine HCl

Free Of

High Fructose Corn Syrup

Alcohol

Artificial Dyes & Flavors

Fall Asleep Fast

Non-habit Forming

Soothing Berry

Not for colds or for pain

12 FL OZ (354 mL)